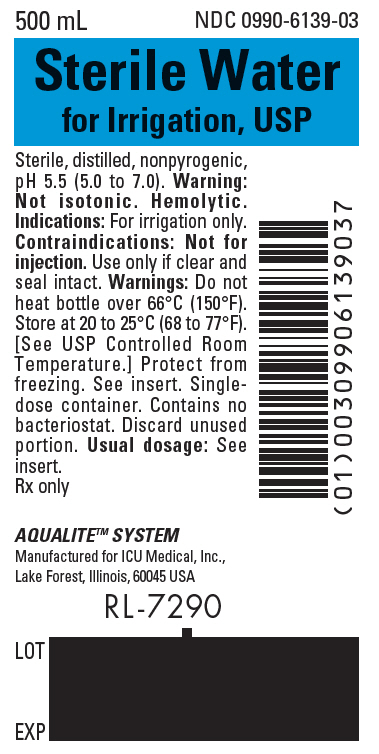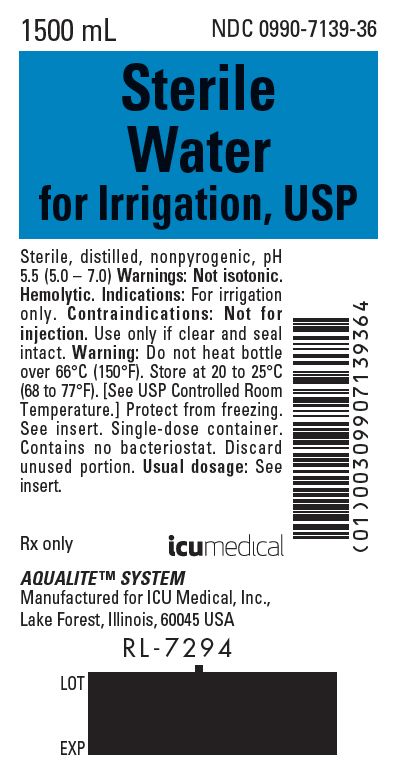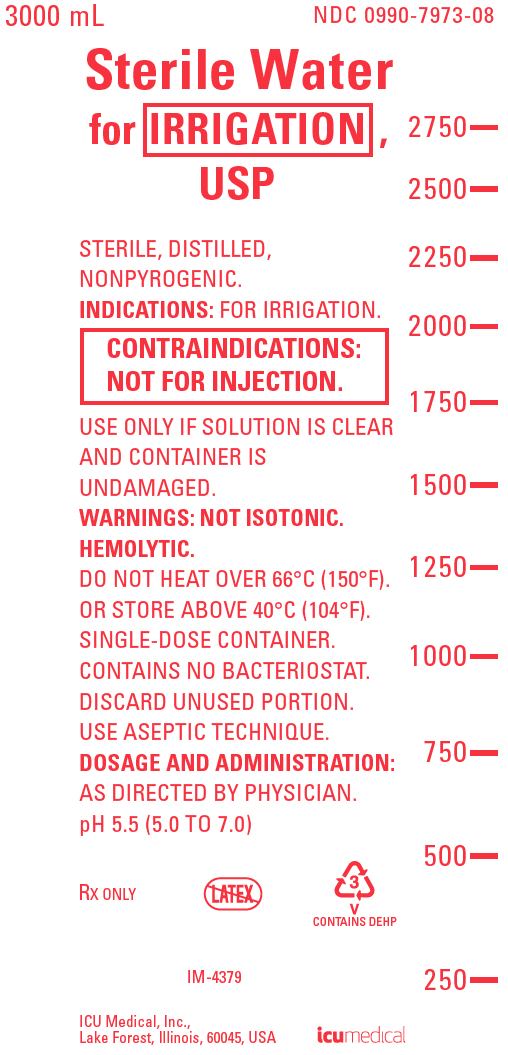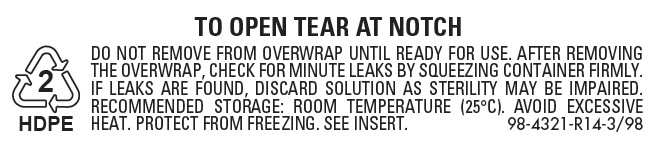 DRUG LABEL: Sterile Water
NDC: 0990-6139 | Form: IRRIGANT
Manufacturer: ICU Medical Inc.
Category: prescription | Type: HUMAN PRESCRIPTION DRUG LABEL
Date: 20200619

ACTIVE INGREDIENTS: WATER 1 mL/1 mL

Sterile Water for Irrigation, USP

FOR ALL GENERAL IRRIGATION, WASHING, RINSING AND DILUTION PURPOSES

For Irrigation Only

Not For Injection By Usual Parenteral Routes

Flexible Irrigation Container

Semi-rigid Irrigation Container

Rx only

DESCRIPTION

Sterile Water for Irrigation, USP is a sterile, distilled, nonpyrogenic water for injection intended only for sterile irrigation, washing, rinsing and dilution purposes. pH 5.5 (5.0 to 7.0).

Sterile Water for Irrigation, USP contains no bacteriostat, antimicrobial agent or added buffer and is intended for use only as a single-dose or short procedure irrigation. When smaller volumes are required the unused portion should be discarded.

Sterile Water for Irrigation, USP may be classified as a sterile irrigant, wash, rinse, diluent and pharmaceutical vehicle.

Water for Irrigation, USP is chemically designated H2O.

The flexible plastic container is fabricated from a specially formulated polyvinylchloride. Water can permeate from inside the container into the overwrap but not in amounts sufficient to affect the solution significantly.

The semi-rigid container is fabricated from a specially formulated polyolefin. It is a copolymer of ethylene and propylene. The container requires no vapor barrier to maintain the proper drug concentration.

The flexible plastic container is fabricated from a specially formulated polyvinylchloride. Water can permeate from inside the container into the overwrap but not in amounts sufficient to affect the solution significantly. Solutions in contact with the plastic container may leach out certain chemical components from the plastic in very small amounts; however, biological testing was supportive of the safety of the plastic container materials. Exposure to temperatures above 25°C/77°F during transport and storage will lead to minor losses in moisture content. Higher temperatures lead to greater losses. It is unlikely that these minor losses will lead to clinically significant changes within the expiration period.

CLINICAL PHARMACOLOGY

Sterile Water for Irrigation, USP exerts a mechanical cleansing action for sterile irrigation of body cavities, tissues or wounds, indwelling urethral catheters and surgical drainage tubes, and for washing, rinsing or soaking surgical dressings, instruments and laboratory specimens. It also serves as a diluent or vehicle for drugs used for irrigation or other pharmaceutical preparations.

Water is an essential constituent of all body tissues and accounts for approximately 70% of total body weight. Average normal adult daily requirement ranges from two to three liters (1.0 to 1.5 liters each for insensible water loss by perspiration and urine production).

Water balance is maintained by various regulatory mechanisms. Water distribution depends primarily on the concentration of electrolytes in the body compartments and sodium (Na^+) plays a major role in maintaining physiologic equilibrium.

INDICATIONS AND USAGE

Sterile Water for Irrigation, USP is indicated for all general irrigation, washing, rinsing and dilution purposes which permit use of sterile, nonpyrogenic, solute-free water.

CONTRAINDICATIONS

NOT FOR INJECTION BY USUAL PARENTERAL ROUTES.

WARNINGS

FOR IRRIGATION ONLY.

This preparation is solute-free and its entry into the circulation will cause hemolysis.

Solutions for urologic irrigation must be used with caution in patients with severe cardiopulmonary or renal dysfunction.

Irrigating fluids used during transurethral prostatectomy have been demonstrated to enter the systemic circulation in relatively large volumes, thus, Sterile Water for Irrigation, USP must be regarded as a systemic drug. Absorption of large amounts of Sterile Water for Irrigation, USP with or without additives can cause fluid and/or solute overloading resulting in dilution of serum electrolyte concentrations, overhydration, congested states or pulmonary edema. The risk of dilutional states is inversely proportional to the electrolyte concentrations of administered solutions. The risk of solute overload causing congested states with peripheral and pulmonary edema is directly proportional to the electrolyte concentrations of such solutions.

Do not heat container over 66°C (150°F).

PRECAUTIONS

Do not use for irrigation that may result in absorption into the blood.

Caution should be observed when solute-free water is used for continuous irrigation or allowed to "dwell" inside body cavities because of possible absorption into the blood stream and the production of intravascular hemolysis and circulatory overload.

Aseptic technique is essential with the use of sterile preparations for irrigation of body cavities, wounds and urethral catheters or for wetting dressings that come in contact with body tissues.

When used as a "pour" irrigation, no part of the contents should be allowed to contact the surface below the outer protected thread area of the semi-rigid wide mouth container.

The flexible container is designed for use with nonvented irrigation sets. When used for irrigation via appropriate irrigation equipment, the administration set should be attached promptly. Unused portions should be discarded and a fresh container of appropriate size used for the start up of each cycle or repeat procedure. For repeated irrigations of urethral catheters, a separate container should be used for each patient.

Do not administer unless water is clear, seal is intact and container is undamaged. Discard unused portion.

Carcinogenesis, Mutagenesis, Impairment of Fertility:

Studies with Sterile Water for Irrigation, USP have not been performed to evaluate carcinogenic potential, mutagenic potential, or effects on fertility.

Nursing Mothers:

Caution should be exercised when Sterile Water for Irrigation, USP is administered to a nursing woman.

Pregnancy: Teratogenic Effects.

Pregnancy Category C. Animal reproduction studies have not been conducted with Sterile Water for Irrigation, USP. It is also not known whether Sterile Water for Irrigation, USP can cause fetal harm when administered to a pregnant woman or can affect reproduction capacity. Sterile Water for Irrigation, USP should be given to a pregnant woman only if clearly needed.

Pediatric Use:

Safety and effectiveness in pediatric patients have not been established.

ADVERSE REACTIONS

Possible adverse effects arising from the irrigation of body cavities, tissues, or indwelling catheters and tubes are completely avoidable when proper procedures are followed. Displaced catheters or drainage tubes can lead to irrigation or infiltration of unintended structures or cavities. Excessive volume or pressure during irrigation of closed cavities may cause undue distention or disruption of tissues. Accidental contamination from careless technique may transmit infection.

Should any adverse reaction occur, discontinue the irrigant, evaluate the patient, institute appropriate therapeutic countermeasures and save the remainder of the fluid for examination, if deemed necessary.

OVERDOSAGE

In the event of overhydration or solute overload (if solutes have been added to the irrigation), re-evaluate the patient and institute appropriate corrective measures. (See WARNINGS, PRECAUTIONS and ADVERSE REACTIONS.)

DOSAGE AND ADMINISTRATION

The dose is dependent upon the capacity or surface area of the structure to be irrigated and the nature of the procedure. When used as a diluent or vehicle for drugs, the manufacturer's recommendations should be followed.

Drug Interactions

Additives may be incompatible. Consult with pharmacist, if available. When introducing additives, use aseptic technique, mix thoroughly and do not store.

Parenteral drug products should be inspected visually for particulate matter and discoloration prior to administration, whenever solution container permits. (See PRECAUTIONS.)

HOW SUPPLIED

NDC No. | Product | Container Size (mL) | Container Type
0409-6139-22 [Manufactured for ICU Medical, Inc., Lake Forest, Illinois, 60045, USA] 0990-6139-22 | Sterile Water for Irrigation USP | 250 | Semi-Rigid Irrigation
0409-6139-03 0990-6139-03 | Sterile Water for Irrigation USP | 500 | Semi-Rigid Irrigation
0409-7139-09 0990-7139-09 | Sterile Water for Irrigation USP | 1000 | Semi-Rigid Irrigation
0409-7139-36 0990-7139-36 | Sterile Water for Irrigation USP | 1500 | Semi-Rigid Irrigation
0409-7973-05 [Manufactured by ICU Medical, Inc., Lake Forest, Illinois, 60045, USA] 0990-7973-05 | Sterile Water for Irrigation USP | 1000 | Flexible Irrigation
0409-7973-07 0990-7973-07 | Sterile Water for Irrigation USP | 2000 | Flexible Irrigation
0409-7973-08 0990-7973-08 | Sterile Water for Irrigation USP | 3000 | Flexible Irrigation

ICU Medical is transitioning NDC codes from the "0409" to a "0990" labeler code. Both NDC codes are expected to be in the market for a period of time.

Store at 20 to 25°C (68 to 77°F). [See USP Controlled Room Temperature.] Protect from freezing.

Revised: July, 2018

ICU Medical, Inc., Lake Forest, Illinois, 60045, USA
EN-4662

PRINCIPAL DISPLAY PANEL - 500 mL Bottle Label

500 mL
NDC 0990-6139-03

Sterile Water
for Irrigation, USP

Sterile, distilled, nonpyrogenic,
pH 5.5 (5.0 to 7.0). Warning:
Not isotonic. Hemolytic.
Indications: For irrigation only.
Contraindications: Not for
injection. Use only if clear and
seal intact. Warnings: Do not
heat bottle over 66°C (150°F).
Store at 20 to 25°C (68 to 77°F).
[See USP Controlled Room
Temperature.] Protect from
freezing. See insert. Single-
dose container. Contains no
bacteriostat. Discard unused
portion. Usual dosage: See
insert.
Rx only

AQUALITE™ SYSTEM
Manufactured for ICU Medical, Inc.,
Lake Forest, Illinois, 60045 USA

RL-7290

LOT

EXP

PRINCIPAL DISPLAY PANEL - 1500 mL Bottle Label

1500 mL
NDC 0990-7139-36

Sterile
Water
for Irrigation, USP

Sterile, distilled, nonpyrogenic, pH
5.5 (5.0 – 7.0) Warnings: Not isotonic.
Hemolytic. Indications: For irrigation
only. Contraindications: Not for
injection. Use only if clear and seal
intact. Warning: Do not heat bottle
over 66°C (150°F). Store at 20 to 25°C
(68 to 77°F). [See USP Controlled Room
Temperature.] Protect from freezing.
See insert. Single-dose container.
Contains no bacteriostat. Discard
unused portion. Usual dosage: See
insert.

Rx only

icumedical

AQUALITE™ SYSTEM
Manufactured for ICU Medical, Inc.,
Lake Forest, Illinois, 60045 USA

RL-7294

LOT

EXP

PRINCIPAL DISPLAY PANEL - 3000 mL Bag Label

3000 mL
NDC 0990-7973-08

Sterile Water
for IRRIGATION,
USP

STERILE, DISTILLED,
NONPYROGENIC.
INDICATIONS: FOR IRRIGATION.
CONTRAINDICATIONS:
NOT FOR INJECTION.
USE ONLY IF SOLUTION IS CLEAR
AND CONTAINER IS
UNDAMAGED.
WARNINGS: NOT ISOTONIC.
HEMOLYTIC.
DO NOT HEAT OVER 66°C (150°F).
OR STORE ABOVE 40°C (104°F).
SINGLE-DOSE CONTAINER.
CONTAINS NO BACTERIOSTAT.
DISCARD UNUSED PORTION.
USE ASEPTIC TECHNIQUE.
DOSAGE AND ADMINISTRATION:
AS DIRECTED BY PHYSICIAN.
pH 5.5 (5.0 TO 7.0)

RX ONLY

3
V
CONTAINS DEHP

IM-4379

ICU Medical, Inc.,
Lake Forest, Illinois, 60045, USA

icumedical

PRINCIPAL DISPLAY PANEL - 3000 mL Bag Overwrap

2
HDPE

TO OPEN TEAR AT NOTCH

DO NOT REMOVE FROM OVERWRAP UNTIL READY FOR USE. AFTER REMOVING
THE OVERWRAP, CHECK FOR MINUTE LEAKS BY SQUEEZING CONTAINER FIRMLY.
IF LEAKS ARE FOUND, DISCARD SOLUTION AS STERILITY MAY BE IMPAIRED.
RECOMMENDED STORAGE: ROOM TEMPERATURE (25°C). AVOID EXCESSIVE
HEAT. PROTECT FROM FREEZING. SEE INSERT.
98-4321-R14-3/98